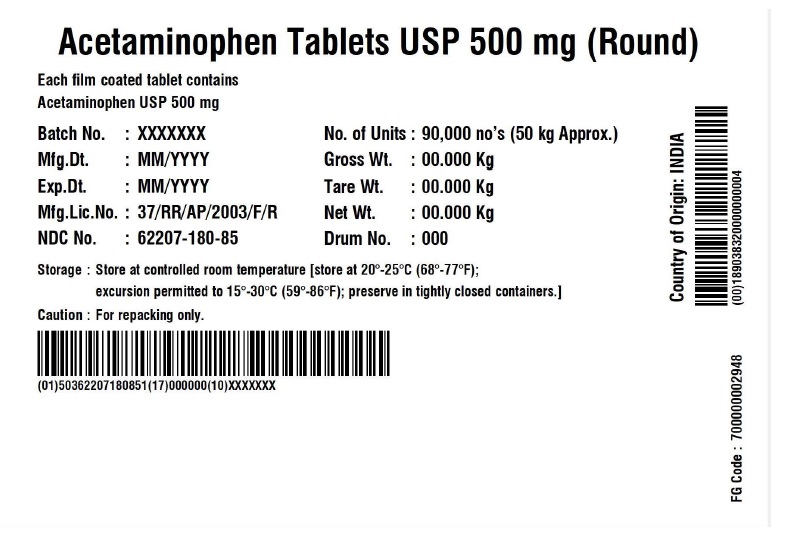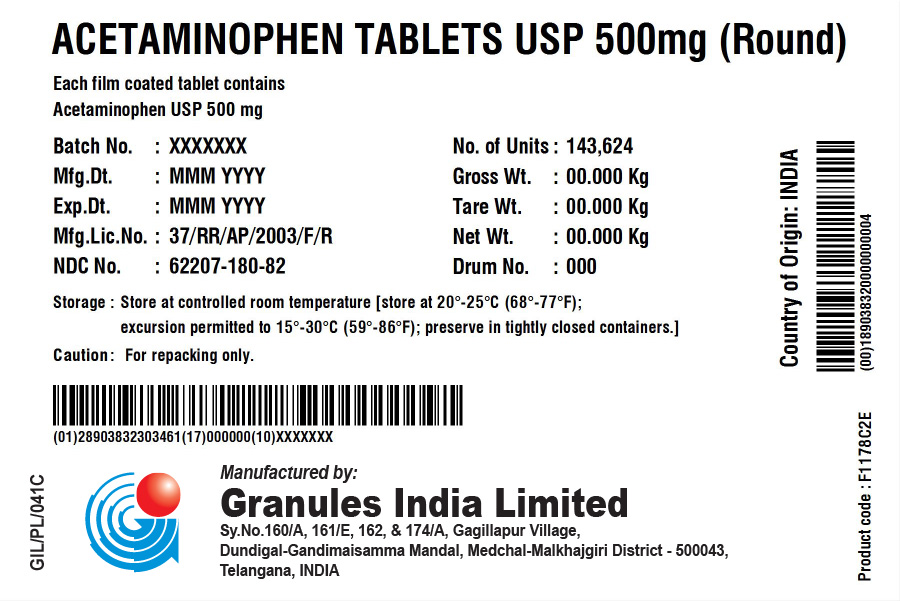 DRUG LABEL: Acetaminophen 500 mg
NDC: 62207-180 | Form: TABLET
Manufacturer: Granules India Limited
Category: otc | Type: HUMAN OTC DRUG LABEL
Date: 20251124

ACTIVE INGREDIENTS: ACETAMINOPHEN 500 mg/1 1
INACTIVE INGREDIENTS: HYPROMELLOSE, UNSPECIFIED; STARCH, CORN; POVIDONE K30; STEARIC ACID; SODIUM STARCH GLYCOLATE TYPE A POTATO; POLYETHYLENE GLYCOL, UNSPECIFIED

Acetaminophen tablets USP 500 mg (Round)